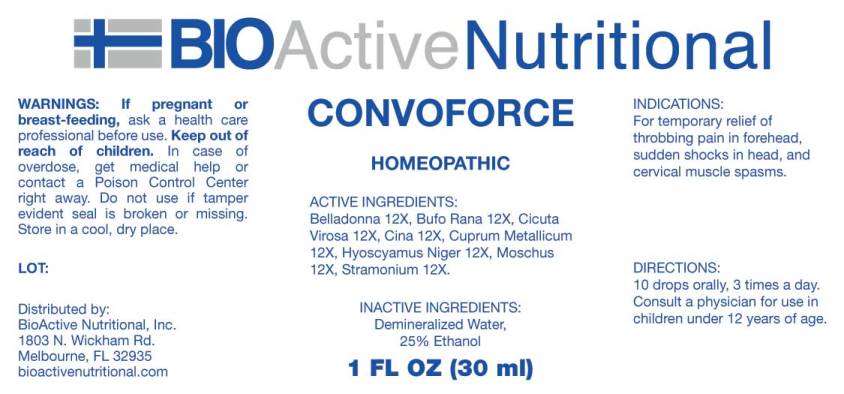 DRUG LABEL: Convoforce
NDC: 43857-0361 | Form: LIQUID
Manufacturer: BioActive Nutritional, Inc.
Category: homeopathic | Type: HUMAN OTC DRUG LABEL
Date: 20240828

ACTIVE INGREDIENTS: ATROPA BELLADONNA 12 [hp_X]/1 mL; BUFO BUFO CUTANEOUS GLAND 12 [hp_X]/1 mL; CICUTA VIROSA ROOT 12 [hp_X]/1 mL; ARTEMISIA CINA PRE-FLOWERING TOP 12 [hp_X]/1 mL; COPPER 12 [hp_X]/1 mL; HYOSCYAMUS NIGER 12 [hp_X]/1 mL; MOSCHUS MOSCHIFERUS MUSK SAC RESIN 12 [hp_X]/1 mL; DATURA STRAMONIUM 12 [hp_X]/1 mL
INACTIVE INGREDIENTS: WATER; ALCOHOL

DRUG FACTS:

ACTIVE INGREDIENTS:

Belladonna 12X, Bufo Rana 12X, Cicuta Virosa 12X, Cina 12X, Cuprum Metallicum 12X, Hyoscyamus Niger 12X, Moschus 12X, Stramonium 12X.

INDICATIONS:

For temporary relief of throbbing pain in forehead, sudden shocks in head, and cervical muscle spasms.

WARNINGS:

If pregnant or breast-feeding, ask a health care professional before use.

Keep out of reach of children. In case of overdose, get medical help or contact a Poison Control Center right away.

Do not use if tamper evident seal is broken or missing.

Store in cool, dry place.

Keep out of reach of children. In case of overdose, get medical help or contact a Poison Control Center right away.

DIRECTIONS:

10 drops orally, 3 times a day. Consult a physician for use in children under 12 years of age.

INDICATIONS:

For temporary relief of throbbing pain in forehead, sudden shocks in head, and cervical muscle spasms.

INACTIVE INGREDIENTS:

Demineralized Water, 25% Ethanol

QUESTIONS:

Distributed by:

BioActive Nutritional, Inc.

1803 N. Wickham Rd.

Melbourne, FL 32935

bioactivenutritional.com

PACKAGE LABEL DISPLAY:

BioActive Nutritional

CONVOFORCE

Homeopathic

1 FL OZ (30 ml)